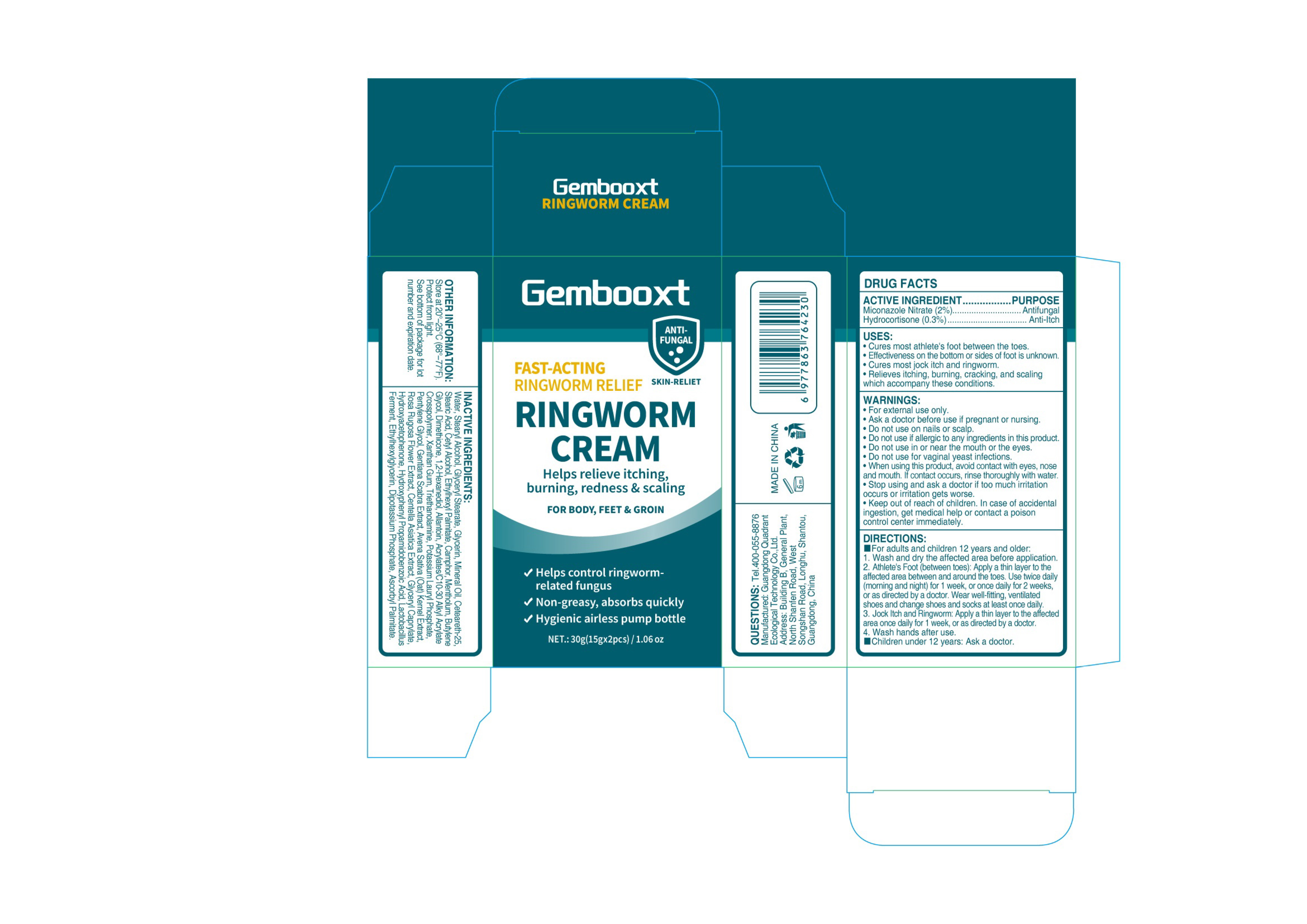 DRUG LABEL: Gembooxt RINGWORM Cream
NDC: 76986-020 | Form: CREAM
Manufacturer: Guangdong Quadrant Ecological Technology Co., Ltd.
Category: otc | Type: HUMAN OTC DRUG LABEL
Date: 20251219

ACTIVE INGREDIENTS: MICONAZOLE NITRATE 0.02 g/1 g; HYDROCORTISONE 0.003 g/1 g
INACTIVE INGREDIENTS: STEARIC ACID; ETHYLHEXYL PALMITATE; GENTIANA SCABRA WHOLE; GLYCERYL STEARATE; GLYCERIN; MINERAL OIL; ASCORBYL PALMITATE; GLYCERYL CAPRYLATE; CENTELLA ASIATICA TRITERPENOIDS; WATER; DIBASIC POTASSIUM PHOSPHATE; XANTHAN GUM; PENTYLENE GLYCOL; CAMPHOR (SYNTHETIC); LACTOBACILLUS REUTERI F275 STRAIN; HYDROXYPHENYL PROPAMIDOBENZOIC ACID; ROSA RUGOSA FLOWER; 1,2-HEXANEDIOL; ALLANTOIN; ACRYLATES/C10-30 ALKYL ACRYLATE CROSSPOLYMER (60000 MPA.S); ETHYLHEXYLGLYCERIN; POTASSIUM LAURYL PHOSPHATE; TRIETHANOLAMINE; CETYL ALCOHOL; STEARYL ALCOHOL; CETEARETH-25; MENTHOL; OAT; DIMETHICONE

76986-020 Gembooxt RINGWORM CREAM

ACTIVE INGREDIENT

Miconazole Nitrate (2%)

Hydrocortisone (0.3%)

PURPOSE

Antifungal, Anti-ltch

INDICATIONS AND USAGE

Cures most athlete's foot between the toes.
Effectiveness on the bottom or sides of foot is unknown
Cures most jock itch and ringworm.
Relieves itching, burning, cracking, and scaling which accompany these conditions.

WARNINGS

For external use only.

Do not use on nails or scalp
Do not use if allergic to any ingredients in this product
Do not use in or near the mouth or the eyes.
Do not use for vaginal yeast infections

Ask a doctor before use if pregnant or nursing.
When using this product, avoid contact with eyes, nose and mouth. lf contact occurs, rinse thoroughly with water

STOP USE

Stop using and ask a doctor if too much irritation occurs or irritation gets worse.

Keep out of reach of children. In case of accidental ingestion, get medical help or contact a poison control center immediately

DOSAGE AND ADMINISTRATION

For adults and children 12 years and older.
1. Wash and dry the affected area before application.
2. Athlete's Foot (between toes): Apply a thin layer to the affected area between and around the toes. Use twice daily(morning and night) for 1 week, or once daily for 2 weeks.or as directed by a doctor. Wear well-fitting, ventilated shoes and change shoes and socks at least once daily.
3. Jock ltch and Ringworm: Apply a thin layer to the affectedarea once daily for 1 week, or as directed by a doctor.
4. Wash hands after use.
Children under 12 years: Ask a doctor.

INACTIVE INGREDIENT

CETYL ALCOHOL
STEARYL ALCOHOL
GLYCERYL STEARATE
GLYCERIN
MINERAL OIL
CETEARETH-25

ETHYLHEXYL PALMITATE

CAMPHOR
MENTHOLUM
GENTIANA SCABRA EXTRACT

CENTELLA ASIATICA EXTRACT

AVENA SATIVA (OAT) KERNEL EXTRACT
ROSA RUGOSA FLOWER EXTRACT
LACTOBACILLUS FERMENT

DIMETHICONE
GLYCERYL CAPRYLATE

ETHYLHEXYLGLYCERIN
1,2-HEXANEDIOL

ALLANTOIN
POTASSIUM LAURYL PHOSPHATE

DIPOTASSIUM PHOSPHATE

ACRYLATES/C10-30 ALKYL ACRYLATE CROSSPOLYMER
XANTHAN GUM
BUTYLENE GLYCOL

PENTYLENE GLYCOL
HYDROXYPHENYL PROPAMIDOBENZOIC ACID
ASCORBYL PALMITATE
TRIETHANOLAMINE